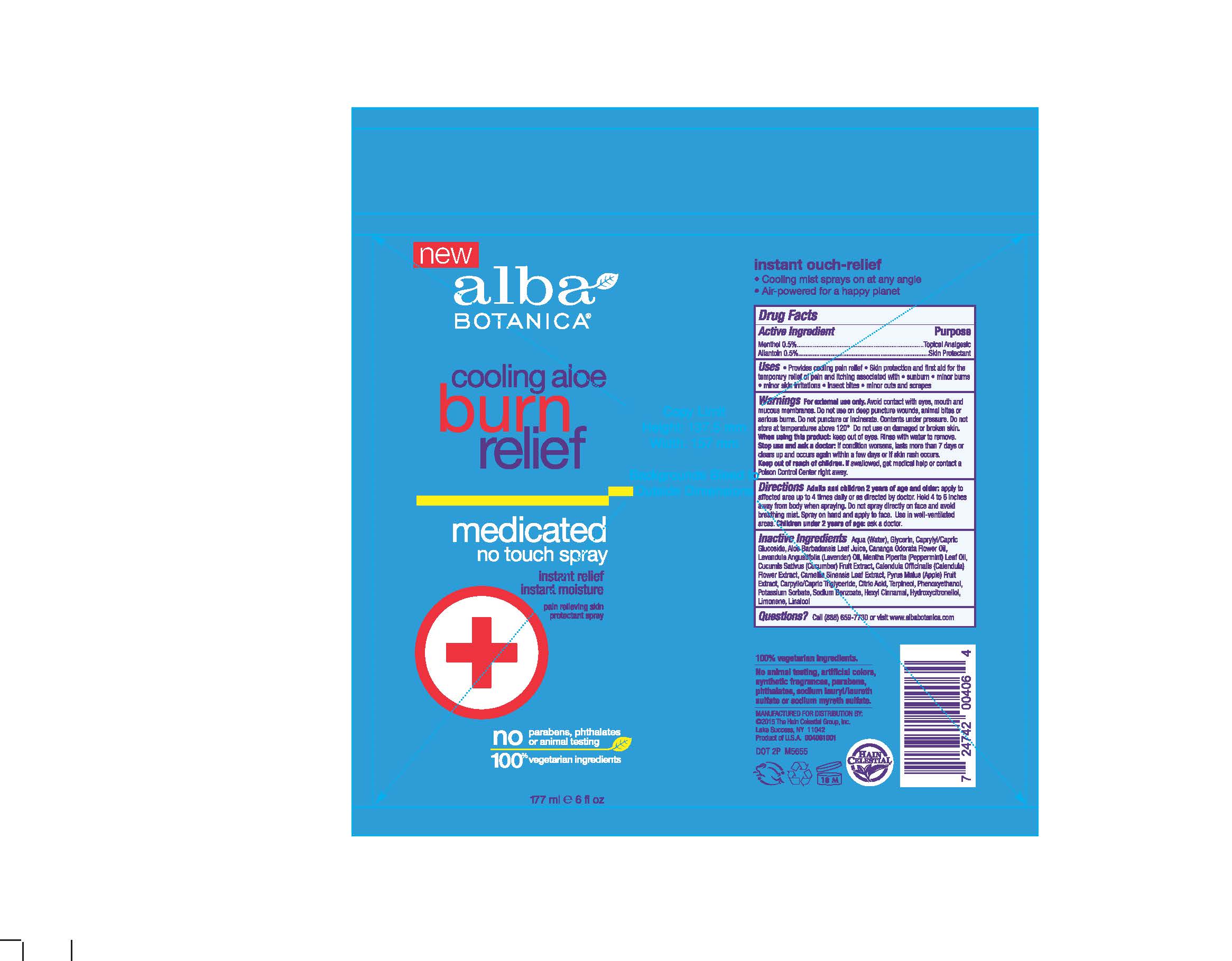 DRUG LABEL: AL0040600 Alba Cooling Aloe Burn Relief
NDC: 61995-2406 | Form: SPRAY
Manufacturer: The Hain Celestial Group, Inc
Category: otc | Type: HUMAN OTC DRUG LABEL
Date: 20210205

ACTIVE INGREDIENTS: ALLANTOIN 0.5 g/100 g; MENTHOL 0.5 g/100 g
INACTIVE INGREDIENTS: ALOE VERA LEAF; CANANGA OIL; CALENDULA OFFICINALIS FLOWER; APPLE; WATER; GLYCERIN; CAPRYLYL/CAPRYL OLIGOGLUCOSIDE; LAVENDER OIL; CUCUMBER; TERPINEOL; PHENOXYETHANOL; POTASSIUM SORBATE; HYDROXYCITRONELLOL; LIMONENE, (+)-; LINALOOL, (+/-)-; .ALPHA.-HEXYLCINNAMALDEHYDE; PEPPERMINT OIL; SODIUM BENZOATE; MEDIUM-CHAIN TRIGLYCERIDES; CITRIC ACID MONOHYDRATE; GREEN TEA LEAF

Alba Botanica Cooling Aloe Burn Relief Spray

ACTIVE INGREDIENT

Allantoin 0.5%

Menthol 0.5%

PURPOSE

Mentol - Topical Analgetic

Allantoin - Skin Protectant

INDICATIONS AND USAGE

- Provides cooling pain relieve
- Skin protection and first aid for the temporary relief of pain and itching associated with sunburn, minor burns, minor skin irritations, insect bites, minor cuts and scrapes

WARNINGS

For external use only. Avoid contact with eyes, mouth and mucous membranes. Do not use on deep puncture wounds, animal bites or serious burns. Do not puncture or incinerate. Contents under preassure .Do not store at temperature above 120°. Do not use on damaged or broken skin. When using this product keep out of eyes. Rinse with water to remove. Stop use and ask doctor if condition worsens, lasts more than 7days or clears up and occurs again in within a few days or if skin rash occurs.

Keep out of reach of children. If swallowed get medical help or contact Poison Center right away.

DOSAGE AND ADMINISTRATION

Adults and children 2 years old and older: apply to affected area up to 4 times daily or as directed by doctor. Hold 4-6 inches away from body when spraying. Do not spray directly on face and avoid breathing mist. Sprayon hand and apply to face.Use in well-ventiled area. Children under 2 years of age : ask a doctor.

INACTIVE INGREDIENT

Aquq (Water),Glycerin, Caprylyl/Capric Glucoside, Aloe Barbadensis Leaf Juice, Cananga Odarata Flower Oil, Mentha Piperita (Peppermint) Oil, Cucumis Sativus (Cucumber) Fruit Extract, Calendula Officinalis Flower Extract, Camellia Sinensis Leaf Extract, Pyrus Malus (Apple) Fruit Extract, Caprylic/Capric Trigluceride, Citric Acid, Terpineol, Phenoxyethanol, Potassium Sorbate, Sodium Benzoate, Hexyl Cinnamal, Hydroxycitronellol, Limonene, Linalool.

QUESTIONS

Questions? Visit www.albabotanica.com or call 888-659-7730